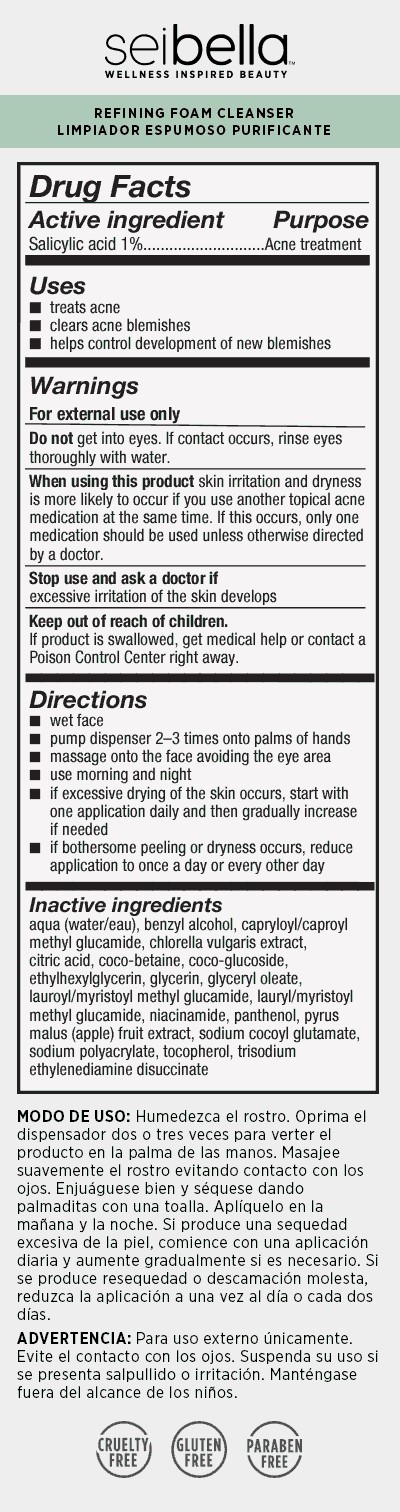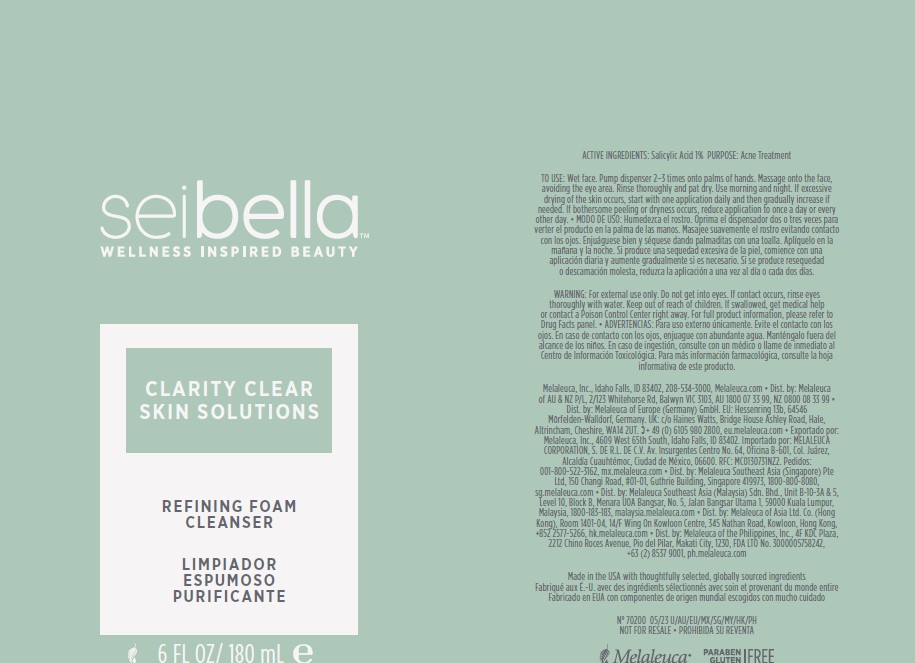 DRUG LABEL: Sei Bella Clarity Clear Refining Foaming Cleanser
NDC: 54473-401 | Form: LIQUID
Manufacturer: Melaleuca, Inc.
Category: otc | Type: HUMAN OTC DRUG LABEL
Date: 20251231

ACTIVE INGREDIENTS: SALICYLIC ACID 1.8 g/180 mL
INACTIVE INGREDIENTS: WATER; TOCOPHEROL; BENZYL ALCOHOL; PANTHENOL; GLYCERYL OLEATE; CITRIC ACID MONOHYDRATE; GLYCERIN; SODIUM POLYACRYLATE (2500000 MW); APPLE PEEL; COCO-BETAINE; COCO GLUCOSIDE; ETHYLHEXYLGLYCERIN; TRISODIUM ETHYLENEDIAMINE DISUCCINATE; LAUROYL/MYRISTOYL METHYL GLUCAMIDE; SODIUM COCOYL GLUTAMATE; CAPRYLOYL/CAPROYL METHYL GLUCAMIDE; CHLORELLA VULGARIS; NIACINAMIDE

Sei Bella Clarity Clear Refining Foaming Cleanser

Active Ingredients

Salicylic Acid 1%

Purpose

Acne treatment

Uses

- treats acne
- clears acne blemishes
- helps control development of new blemishes

Warnings

For external use only

Do not get into eyes. If contact occurs, rinse eyes thoroughly with water.

When using this product skin irritation and dryness is more likely to occur if you use another topical acne medication at the same time. If this occurs, only one medication should be used unless otherwise directed by a doctor.

Stop use and ask a doctor if excessive irritation of the skin develops.

Keep out of reach of children. If product is swallowed, get medical help or contact a Poison Control Center right away.

Directions

- wet face
- pump dispenser 2-3 times onto palms of hands
- massage onto the face avoiding the eye area
- use morning and night
- if excessive drying of the skin occurs, start with one application daily and then gradually increase if needed
- if bothersome peeling or dryness occurs, reduce application to once a day or every other day

INACTIVE INGREDIENT

Aqua (Water/Eau), Sodium Cocoyl Glutamate, Glycerin, Lauroyl/Myristoyl Methyl Glucamide, Pyrus Malus Fruit Extract, Coco-Betaine, Niacinamide, Panthenol, Salicylic Acid, Sodium Polyacrylate, Benzyl Alcohol, Capryloyl/Caproyl Methyl Glucamide, Coco-Glucoside, Glyceryl Oleate, Citric Acid, Ethylhexylglycerin, Trisodium Ethylenediamine Disuccinate, Chlorella Vulgaris, Extract, Tocopherol